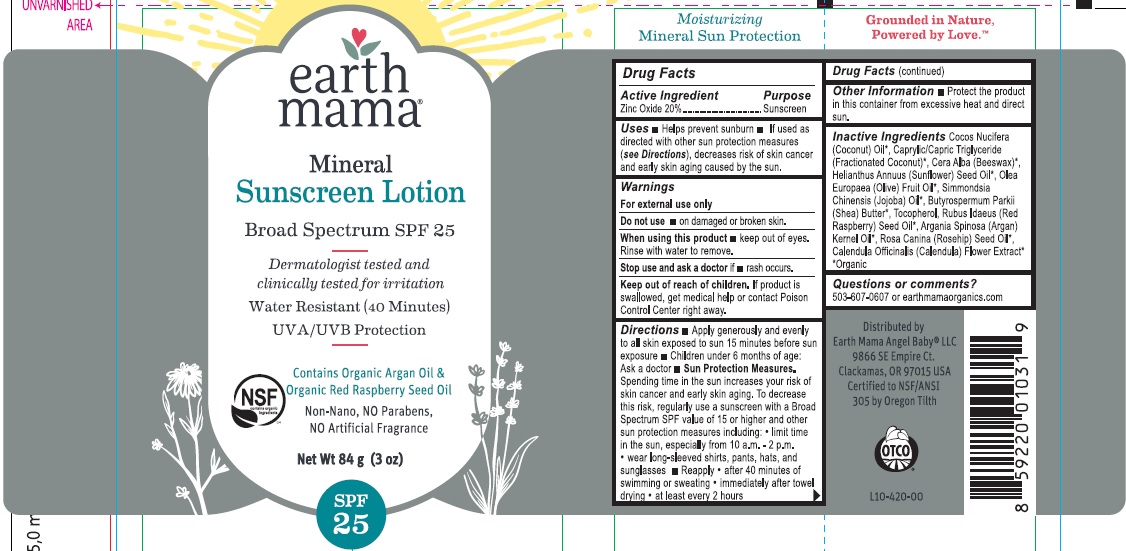 DRUG LABEL: SUNSCREEN
NDC: 62932-168 | Form: OINTMENT
Manufacturer: Private Label Select Ltd CO
Category: otc | Type: HUMAN OTC DRUG LABEL
Date: 20181101

ACTIVE INGREDIENTS: ZINC OXIDE 20 g/100 g
INACTIVE INGREDIENTS: SIMMONDSIA CHINENSIS SEED WAX; SHEA BUTTER; TOCOPHEROL; RASPBERRY SEED OIL; ARGAN OIL; ROSA CANINA FRUIT OIL; CALENDULA OFFICINALIS FLOWER; HELIANTHUS ANNUUS SEED WAX; OLEA EUROPAEA FRUIT VOLATILE OIL; COCONUT OIL; CAPRYLIC/CAPRIC/LAURIC TRIGLYCERIDE; YELLOW WAX

earth mama Mineral Sunscreen SPF25 Lotion